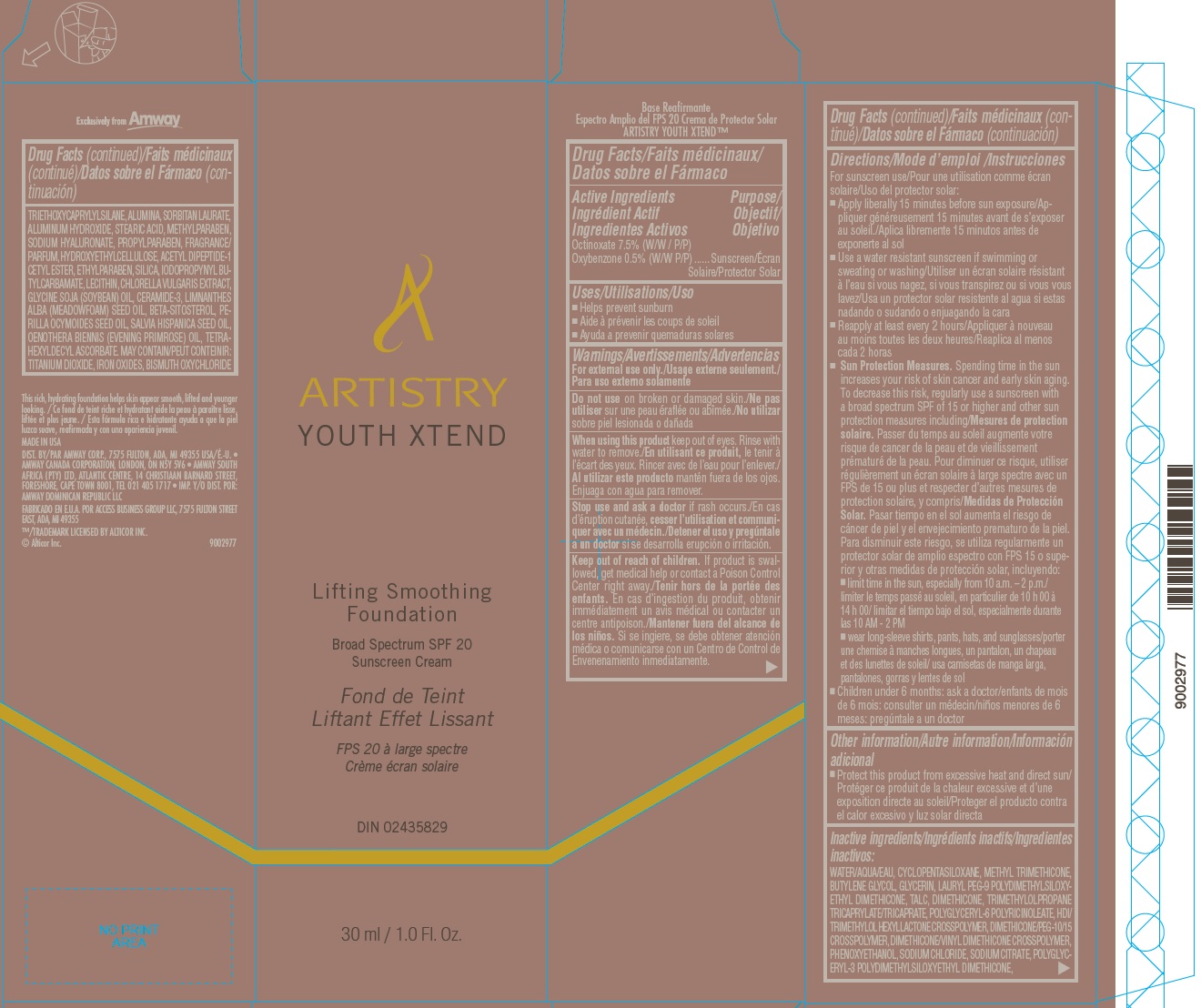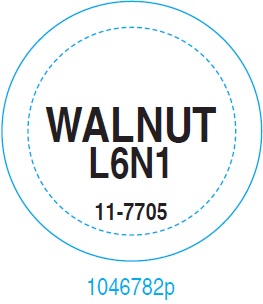 DRUG LABEL: 
                  Artistry Youth Xtend Lifting Smoothing Foundation Shade Walnut

                
                  

NDC: 50390-235 | Form: CREAM
Manufacturer: Amway Corp
Category: otc | Type: HUMAN OTC DRUG LABEL
Date: 20231023

ACTIVE INGREDIENTS: OCTINOXATE 75 mg/1 mL; OXYBENZONE 5 mg/1 mL
INACTIVE INGREDIENTS: WATER; CYCLOMETHICONE 5; METHYL TRIMETHICONE; BUTYLENE GLYCOL; GLYCERIN; LAURYL PEG-9 POLYDIMETHYLSILOXYETHYL DIMETHICONE; TALC; DIMETHICONE; TRIMETHYLOLPROPANE TRICAPRYLATE/TRICAPRATE; POLYGLYCERYL-6 POLYRICINOLEATE; HEXAMETHYLENE DIISOCYANATE/TRIMETHYLOL HEXYLLACTONE CROSSPOLYMER; DIMETHICONE/PEG-10/15 CROSSPOLYMER; PHENOXYETHANOL; SODIUM CHLORIDE; SODIUM CITRATE; TRIETHOXYCAPRYLYLSILANE; ALUMINUM OXIDE; SORBITAN MONOLAURATE; ALUMINUM HYDROXIDE; STEARIC ACID; METHYLPARABEN; HYALURONATE SODIUM; PROPYLPARABEN; HYDROXYETHYL CELLULOSE, UNSPECIFIED; ACETYL TYROSYLARGININE CETYL ESTER; ETHYLPARABEN; SILICON DIOXIDE; IODOPROPYNYL BUTYLCARBAMATE; CHLORELLA VULGARIS; SOYBEAN OIL; CERAMIDE NP; MEADOWFOAM SEED OIL; .BETA.-SITOSTEROL; PERILLA FRUTESCENS SEED OIL; CHIA SEED OIL; EVENING PRIMROSE OIL; TETRAHEXYLDECYL ASCORBATE

Artistry Youth Xtend™ Lifting Smoothing Foundation Shade Walnut – L6N1

Active Ingredients

Octinoxate 7.5% (W/W / P/P)

Oxybenzone 0.5% (W/W P/P)

Purpose

Sunscreen

Uses

- Helps prevent sunburn

Warnings

For external use only

Do not use

on broken or damaged skin

When using this product

keep out of eyes. Rinse with water to remove.

Stop use and ask a doctor

if rash occurs

Keep out of reach of children.

If product is swallowed, get medical help or contact a Poison Control Center right away.

Directions

For suncreen use

- Apply liberally 15 minutes before sun exposure
- Use a water resistant sunscreen if swimming or sweating or washing
- Reapply at least every 2 hours
- Spending time in the sun increases your risk of skin cancer and early skin aging. Sun Protection Measures.
- To decrease this risk, regularly use a sunscreen with a broad spectrum SPF of 15 or higher and other sun protection measures including:
- limit time in the sun, especially from 10 a.m. – 2 p.m.
- wear long-sleeve shirts, pants, hats, and sunglasses
- Children under 6 months: ask a doctor

Other Information

- Protect this product from excessive heat and direct sun

Inactive ingredients

WATER/AQUA/EAU, CYCLOPENTASILOXANE, METHYL TRIMETHICONE, BUTYLENE GLYCOL, GLYCERIN, LAURYL PEG-9 POLYDIMETHYLSILOXYETHYL DIMETHICONE, TALC, DIMETHICONE, TRIMETHYLOLPROPANE TRICAPRYLATE/TRICAPRATE, POLYGLYCERYL-6 POLYRICINOLEATE, HDI/ TRIMETHYLOL HEXYLLACTONE CROSSPOLYMER, DIMETHICONE/PEG-10/15 CROSSPOLYMER, DIMETHICONE/VINYL DIMETHICONE CROSSPOLYMER, PHENOXYETHANOL, SODIUM CHLORIDE, SODIUM CITRATE, POLYGLYCERYL- 3 POLYDIMETHYLSILOXYETHYL DIMETHICONE, TRIETHOXYCAPRYLYLSILANE, ALUMINA, SORBITAN LAURATE, ALUMINUM HYDROXIDE, STEARIC ACID, METHYLPARABEN, SODIUM HYALURONATE, PROPYLPARABEN, FRAGRANCE/ PARFUM, HYDROXYETHYLCELLULOSE, ACETYL DIPEPTIDE-1 CETYL ESTER, ETHYLPARABEN, SILICA, IODOPROPYNYL BUTYLCARBAMATE, LECITHIN, CHLORELLA VULGARIS EXTRACT, GLYCINE SOJA (SOYBEAN) OIL, CERAMIDE-3, LIMNANTHES ALBA (MEADOWFOAM) SEED OIL, BETA-SITOSTEROL, PERILLA OCYMOIDES SEED OIL, SALVIA HISPANICA SEED OIL, OENOTHERA BIENNIS (EVENING PRIMROSE) OIL, TETRAHEXYLDECYL ASCORBATE. MAY CONTAIN/PEUT CONTEINIR: TITANIUM DIOXIDE, IRON OXIDES, BISMUTH OXYCHLORIDE